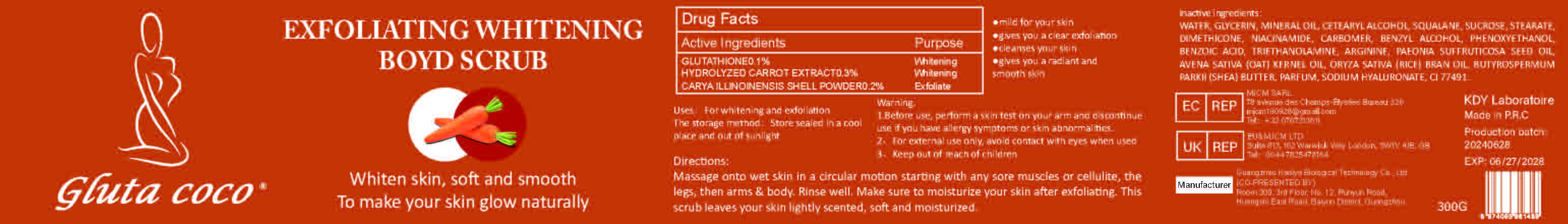 DRUG LABEL: EXFOLIATING WHITENING BOYD SCRUB
NDC: 84423-023 | Form: EMULSION
Manufacturer: Guangzhou Kadiya Biotechnology Co., Ltd.
Category: otc | Type: HUMAN OTC DRUG LABEL
Date: 20240723

ACTIVE INGREDIENTS: CARYA ILLINOINENSIS SHELL 0.3 mg/300 mL; GLUTATHIONE 0.9 mg/300 mL
INACTIVE INGREDIENTS: HYALURONATE SODIUM; RICE BRAN OIL; MINERAL OIL; SUCROSE STEARATE; DIMETHICONE; GLYCERIN; SQUALANE; PHENOXYETHANOL; FERRIC OXIDE RED; OAT KERNEL OIL; WATER; CETOSTEARYL ALCOHOL; NIACINAMIDE; SHEA BUTTER; BENZYL ALCOHOL; TROLAMINE; ARGININE; PAEONIA SUFFRUTICOSA FLOWER OIL; CARBOXYPOLYMETHYLENE

Uses：
For whitening and exfoliation

INACTIVE INGREDIENT

WATER、GLYCERIN、MINERAL OIL、CETEARYL ALCOHOL、SQUALANE、SUCROSE 、STEARATE、DIMETHICONE、NIACINAMIDE、CARBOMER、BENZYL ALCOHOL、PHENOXYETHANOL、BENZOIC ACID、TRIETHANOLAMINE、ARGININE、PAEONIA SUFFRUTICOSA SEED OIL、AVENA SATIVA (OAT) KERNEL OIL、ORYZA SATIVA (RICE) BRAN OIL、BUTYROSPERMUM PARKII (SHEA) BUTTER、PARFUM、SODIUM HYALURONATE、CI 77491

Warning.
1.Before use, perform a skin test on your arm and discontinue use if you have allergy symptoms or skin abnormalities.
2、For external use only, avoid contact with eyes when used
3、Keep out of reach of children

INDICATIONS AND USAGE

Massage onto wet skin in a circular motion starting with any sore muscles or cellulite thelegs, then arms & body. Rinse well. Make sure to moisturize your skin after exfoliating. Thisscrub leaves your skin lightly scented, soft and moisturized.

KEEP OUT OF REACH OF CHILDREN SECTION

Active Ingredients
GLUTATHIONE 0.1%
HYDROLYZED CARROT EXTRACT 0.3%
CARYA ILLINOINENSIS SHELL POWDER 0.2%

DOSAGE AND ADMINISTRATION

Massage onto wet skin in a circular motion starting with any sore muscles or cellulite thelegs, then arms & body. Rinse well. Make sure to moisturize your skin after exfoliating. Thisscrub leaves your skin lightly scented, soft and moisturized.

Drug Facts
Active Ingredients
GLUTATHIONE 0.1%
HYDROLYZED CARROT EXTRACT 0.3%
CARYA ILLINOINENSIS SHELL POWDER 0.2%
Uses：
For whitening and exfoliation
The storage method：
Store sealed in a cool place and out of sunlight
Warning.
1.Before use, perform a skin test on your arm and discontinue use if you have allergy symptoms or skin abnormalities.
2、For external use only, avoid contact with eyes when used
3、Keep out of reach of children
Inactive ingredients：
WATER、GLYCERIN、MINERAL OIL、CETEARYL ALCOHOL、SQUALANE、SUCROSE 、STEARATE、DIMETHICONE、NIACINAMIDE、CARBOMER、BENZYL ALCOHOL、PHENOXYETHANOL、BENZOIC ACID、TRIETHANOLAMINE、ARGININE、PAEONIA SUFFRUTICOSA SEED OIL、AVENA SATIVA (OAT) KERNEL OIL、ORYZA SATIVA (RICE) BRAN OIL、BUTYROSPERMUM PARKII (SHEA) BUTTER、PARFUM、SODIUM HYALURONATE、CI 77491